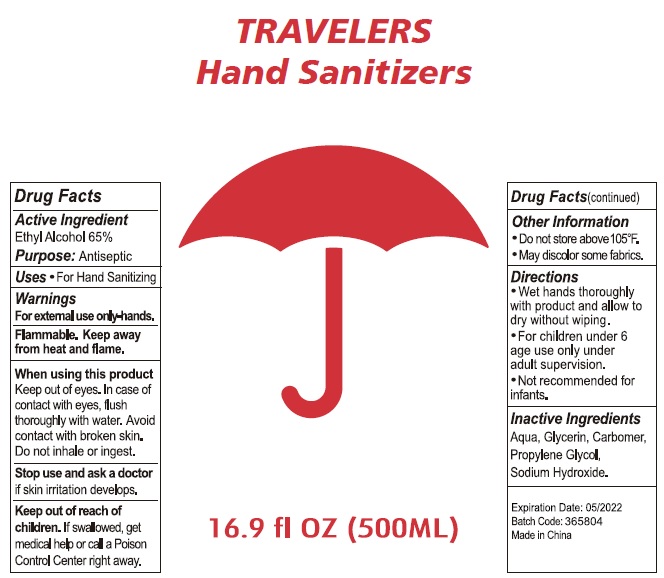 DRUG LABEL: Travelers Hand Sanitizers
NDC: 74274-012 | Form: SOLUTION
Manufacturer: Huizhou Bliss Commodity Co., Ltd
Category: otc | Type: HUMAN OTC DRUG LABEL
Date: 20200429

ACTIVE INGREDIENTS: ALCOHOL 65 mL/100 mL
INACTIVE INGREDIENTS: WATER; CARBOMER INTERPOLYMER TYPE A (ALLYL SUCROSE CROSSLINKED); GLYCERIN; PROPYLENE GLYCOL; SODIUM HYDROXIDE

Active ingredient

Ethyl Alcohol 65%

Purpose

Antiseptic

Use

For hand Sanitizing

KEEP OUT OF REACH OF CHILDREN

if swallowed, get medical help or contact a Poison Control Center right away.

warnings:

Flamable, keep away from heat and flame.

For external use only hands.

When using this product

keep out of eyes. In case of contact with eye, flush thoroughly with water. Avoid contact with broken skin. Do not inhale or ingest.

Stop use and ask a doctor

If irritation develops.

Directions

- Wet hands thoroughly with product and allow to dry without wiping.
- For children under 6 age use only under adult supervision.
- Not recommended for infants.

Other Information:

- Dn not store above 105℉.
- may discolor some fabrics.

Inactive ingredients

Aqua, glycerin, carbomer, propyene glycol, sodium hydroxide